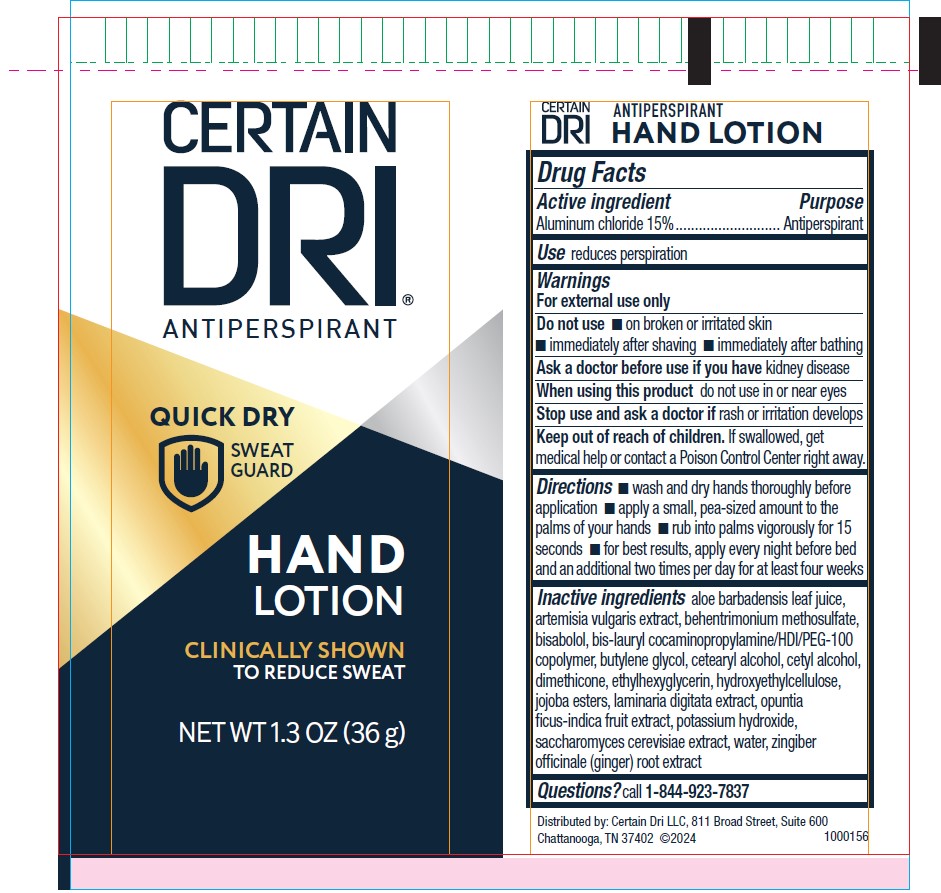 DRUG LABEL: Certain Dri Antiperspirant Hand-Lotion
NDC: 69693-723 | Form: LOTION
Manufacturer: Clarion Brands, LLC
Category: otc | Type: HUMAN OTC DRUG LABEL
Date: 20251223

ACTIVE INGREDIENTS: ALUMINUM CHLORIDE 0.15 g/100 mL
INACTIVE INGREDIENTS: ALOE VERA LEAF; ARTEMISIA VULGARIS ROOT; BEHENTRIMONIUM METHOSULFATE; LEVOMENOL; THIAMINE BIS-LAURYLSULFATE; BUTYLENE GLYCOL; CETOSTEARYL ALCOHOL; CETYL ALCOHOL; DIMETHICONE; ETHYLHEXYLGLYCERIN; HYDROXYETHYL CELLULOSE, UNSPECIFIED; HYDROLYZED JOJOBA ESTERS (ACID FORM); LAMINARIA DIGITATA; OPUNTIA FICUS-INDICA FRUIT JUICE; POTASSIUM HYDROXIDE; SACCHAROMYCES CEREVISIAE; WATER; GINGER

Drug Facts

Active ingredient

Aluminum chloride 15%

Purpose

Antiperspirant

Use

reduces perspiration

Warnings

For external use only

Do not use

- on broken or irritated skin
- immediately after shaving
- immediately after bathing

Ask a doctor before use if you havekidney disease

When using this product

do not use in or near eyes

Stop use and ask a doctor ifrash or irritation develops

Keep out of reach of children.If swallowed, get medical help or contact a Poison Control Center right away.

Directions

- wash and dry hands thoroughly before application
- apply a small, pea sized amount to the palms of your hands
- rub into palms vigorously for 15 seconds
- for best results, apply every night before bed and an additional two times per day for at least four weeks

Inactive ingredients

aloe barbadensis leaf juice, artemisia vulgarixs extract, behentrimonium methosulfate, bisaolol, bis-laurl cocaminopropylamine/HDI/PEG-100 copolymer, butylene glycol, cetearyl alcohol, cetyl alcohol, dimethicone, ethylhexyglycerin, hydroxyethylcellulose, jojoba esters, laminaria digitata extract, opuntia ficus-indica fruit extract, potassium hydroxide, saccharomyces cerevisiae extract, water, zingiber officinale (ginger) root extract

Questions?

call 1-844-923-7837

PACKAGE LABEL

CERTAIN
DRI®
ANTIPERSPIRANT
QUICK DRY
SWEAT
GUARD
HAND
LOTION
CLINICALLY SHOWN
TO REDUCE SWEAT
NET WT 1.3 OZ (36 g)
Distributed by: Certain Dri LLC, 811 Broad Street, Suite 600
Chattanooga, TN 37402 ©2023
1000156